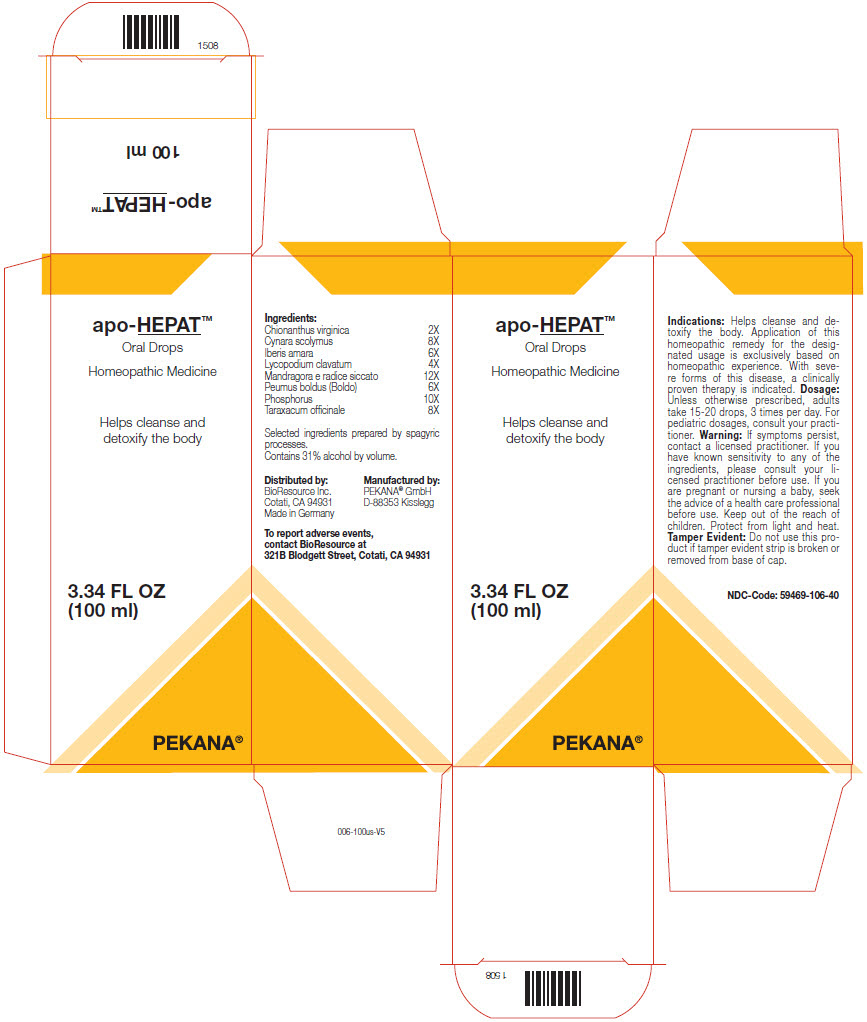 DRUG LABEL: apo-HEPAT
NDC: 59469-106 | Form: SOLUTION/ DROPS
Manufacturer: PEKANA Naturheilmittel GmbH
Category: homeopathic | Type: HUMAN OTC DRUG LABEL
Date: 20221202

ACTIVE INGREDIENTS: CHIONANTHUS VIRGINICUS ROOT BARK 2 [hp_X]/50 mL; Iberis amara Seed 6 [hp_X]/50 mL; Lycopodium clavatum Spore 4 [hp_X]/50 mL; Mandragora officinarum Root 12 [hp_X]/50 mL; Phosphorus 10 [hp_X]/50 mL; Peumus boldus Leaf 6 [hp_X]/50 mL; Cynara scolymus Whole 8 [hp_X]/50 mL; Taraxacum officinale Whole 8 [hp_X]/50 mL
INACTIVE INGREDIENTS: Water; Alcohol

apo-HEPAT™

ACTIVE INGREDIENT

Ingredients:
Chionanthus virginica | 2X
Cynara scolymus | 8X
Iberis amara | 6X
Lycopodium clavatum | 4X
Mandragora e radice siccato | 12X
Peumus boldus (Boldo) | 6X
Phosphorus | 10X
Taraxacum officinale | 8X

Selected ingredients prepared by spagyric processes.

INACTIVE INGREDIENT

Contains 31% alcohol by volume.

Indications

PURPOSE

Helps cleanse and detoxify the body. Application of this homeopathic remedy for the designated usage is exclusively based on homeopathic experience. With severe forms of this disease, a clinically proven therapy is indicated.

Dosage

Unless otherwise prescribed, adults take 15-20 drops, 3 times per day. For pediatric dosages, consult your practitioner.

Warning

If symptoms persist, contact a licensed practitioner. If you have known sensitivity to any of the ingredients, please consult your licensed practitioner before use. If you are pregnant or nursing a baby, seek the advice of a health care professional before use.

Keep out of the reach of children.

STORAGE AND HANDLING

Protect from light and heat.

Tamper Evident

Do not use this product if tamper evident strip is broken or removed from base of cap.

QUESTIONS

To report adverse events, contact BioResource at 321B Blodgett Street, Cotati, CA 94931

Distributed by:
BioResource Inc.
Cotati, CA 94931

Manufactured by:
PEKANA® GmbH
D-88353 Kisslegg

PRINCIPAL DISPLAY PANEL - 100 ml Bottle Box

apo-HEPAT™

Oral Drops
Homeopathic Medicine

Helps cleanse and
detoxify the body

3.34 FL OZ
(100 ml)

PEKANA®